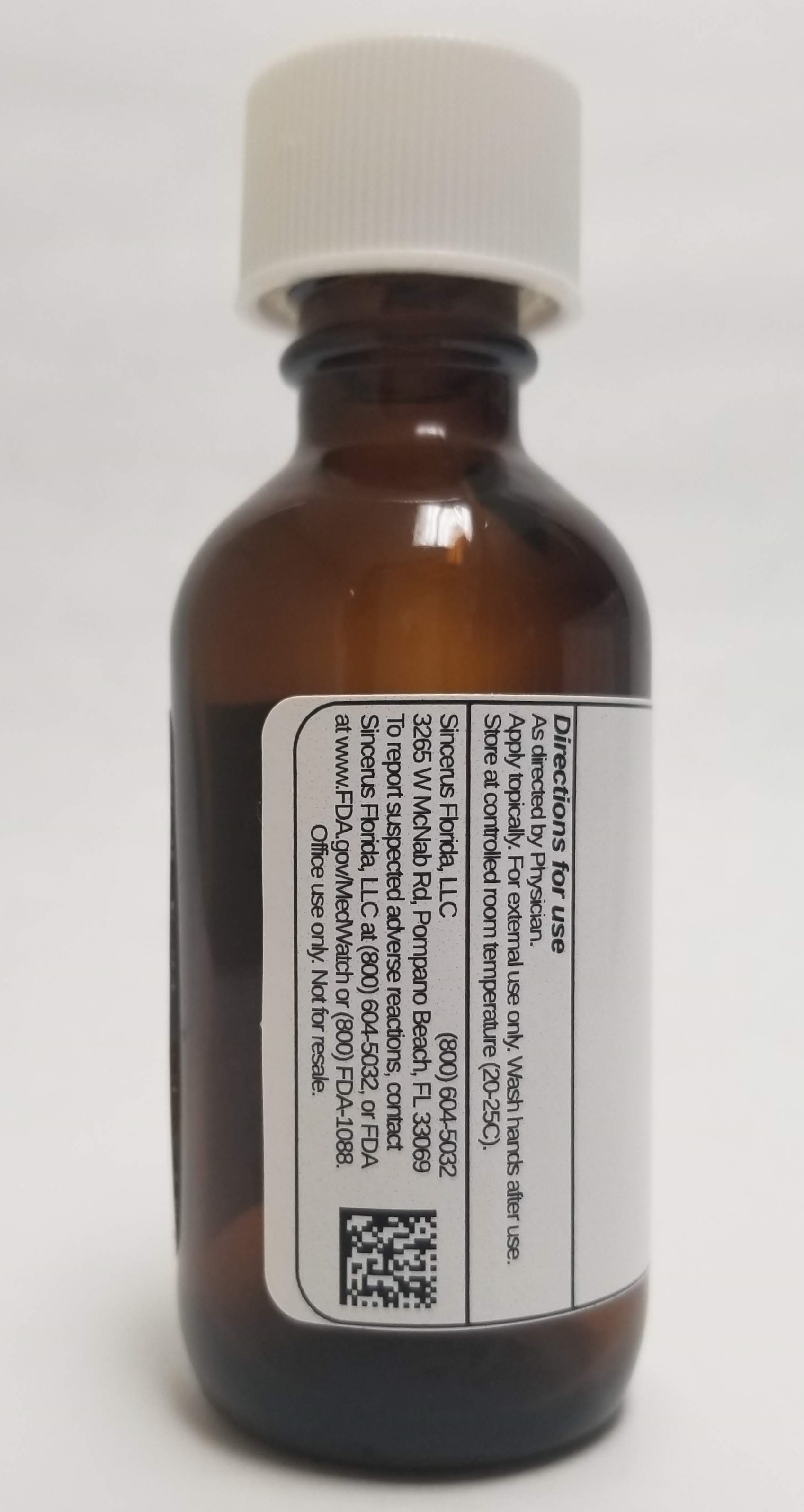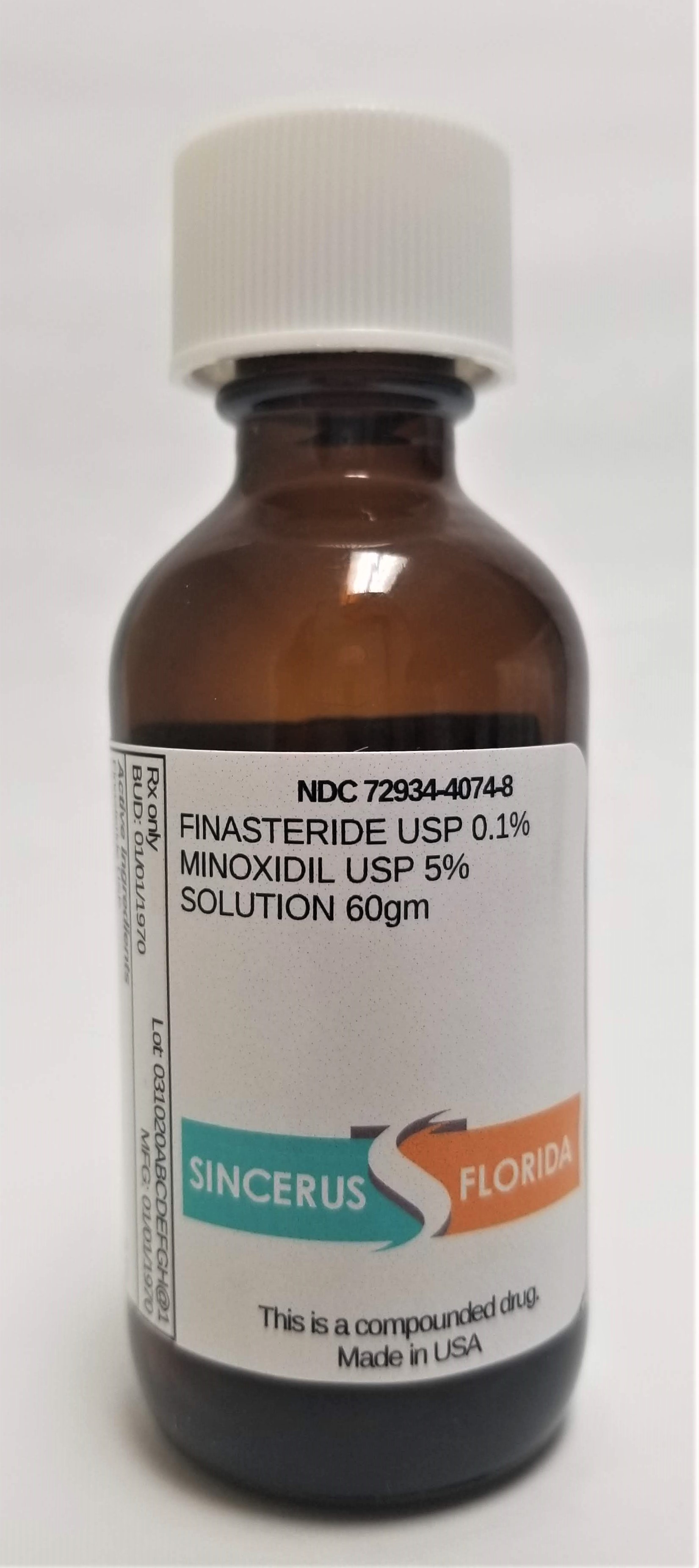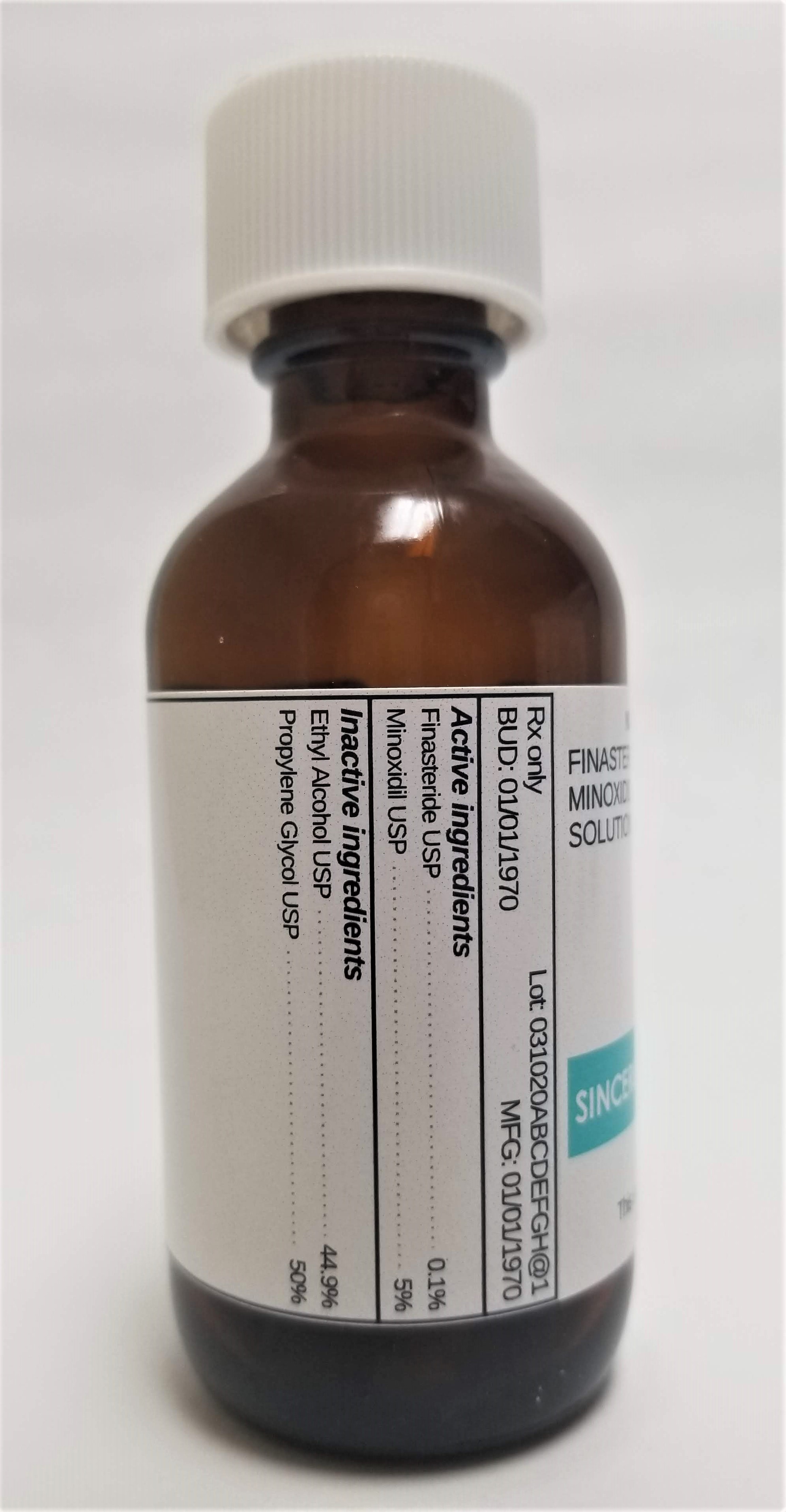 DRUG LABEL: FINASTERIDE 0.1% / MINOXIDIL 5%
NDC: 72934-4074 | Form: SOLUTION
Manufacturer: Sincerus Florida, LLC
Category: prescription | Type: HUMAN PRESCRIPTION DRUG LABEL
Date: 20190508

ACTIVE INGREDIENTS: MINOXIDIL 5 g/100 g; FINASTERIDE 0.1 g/100 g

FINASTERIDE 0.1% / MINOXIDIL 5%